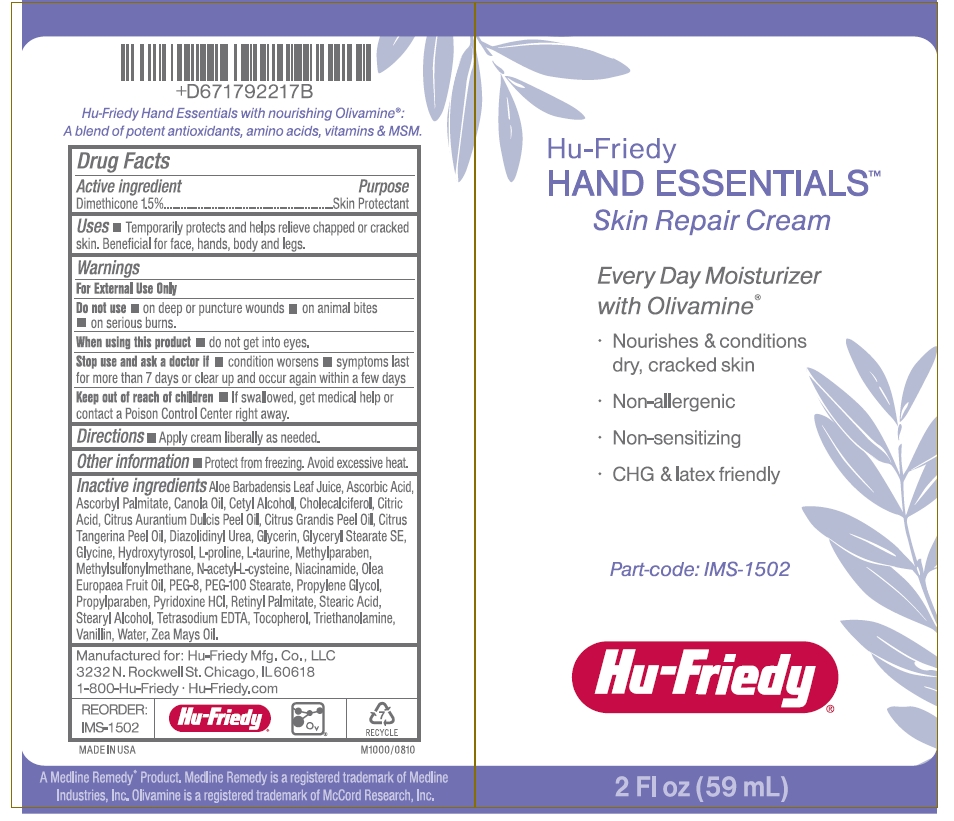 DRUG LABEL: Hand Essentials Skin Repair
NDC: 65626-161 | Form: CREAM
Manufacturer: HU-FRIEDY MFG. CO., INC.
Category: otc | Type: HUMAN OTC DRUG LABEL
Date: 20120329

ACTIVE INGREDIENTS: DIMETHICONE 1.5 mL/100 mL
INACTIVE INGREDIENTS: ALOE VERA LEAF; ASCORBIC ACID; ASCORBYL PALMITATE; CANOLA OIL; CETYL ALCOHOL; CHOLECALCIFEROL; CITRIC ACID MONOHYDRATE; ORANGE OIL; MANDARIN OIL; DIAZOLIDINYL UREA; GLYCERIN; GLYCERYL MONOSTEARATE; GLYCINE; PROLINE; TAURINE; METHYLPARABEN; DIMETHYL SULFONE; ACETYLCYSTEINE; NIACINAMIDE; OLIVE OIL; POLYETHYLENE GLYCOL 400; PEG-100 STEARATE; PROPYLENE GLYCOL; PROPYLPARABEN; PYRIDOXINE HYDROCHLORIDE; VITAMIN A PALMITATE; STEARIC ACID; STEARYL ALCOHOL; EDETATE SODIUM; .ALPHA.-TOCOPHEROL; TROLAMINE; VANILLIN; WATER; CORN OIL

Drug Facts

Active ingredient

Dimethicone 1.5%

Purpose

Skin protectant

Uses

- Temporarily protects and helps relieve chapped or cracked skin. Beneficial for face, hands, body and legs.

Warnings

For External Use Only.

Do not use

- on deep or puncture wounds
- on animal bites
- on serious burns

When using this product

- do not get into eyes.

Stop use and ask a doctor if

- condition worsens
- symptoms last for more than 7 days or clear up and occur again within a few days

Keep out of reach of children.

- If swallowed, get medical help or contact a Poison Control Center right away.

Directions

- Apply cream liberally as needed.

Other information

- Protect from freezing. Avoid excessive heat.

Inactive ingredients

Aloe Barbadensis Leaf Juice, Ascorbic Acid, Ascorbyl Palmitate, Canola Oil, Cetyl Alcohol, Cholecalciferol, Citric Acid, Citrus Aurantium Dulcis Peel Oil, Citrus Grandis Peel Oil, Citrus Tangerina Peel Oil, Diazolidinyl Urea, Glycerin, Glyceryl Stearate SE, Glycine, Hydroxytyrosol, L-proline, L-taurine, Methylparaben, Methylsulfonylmethane, N-acetyl-L-cysteine, Niacinamide, Olea Europaea Fruit Oil, PEG-8, PEG-100 Stearate, Propylene Glycol, Propylparaben, Pyridoxine HCI, Retinyl Palmitate, Stearic Acid, Stearyl Alcohol, Tetrasodium EDTA, Tocopherol, Triethanolamine, Vanillin, Water, Zea Mays Oil.

Package/Label Principal Display Panel

Hu-Friedy

HAND ESSENTIALS

Skin Repair Cream

Every Day Moisturizer

with Olivamine

- Nourishes and conditions dry, cracked skin
- Non-allergenic
- Non-sensitizing
- CHG & latex friendly

Part-code: IMS-1502

Hu-Friedy

2 Fl oz (59 mL)